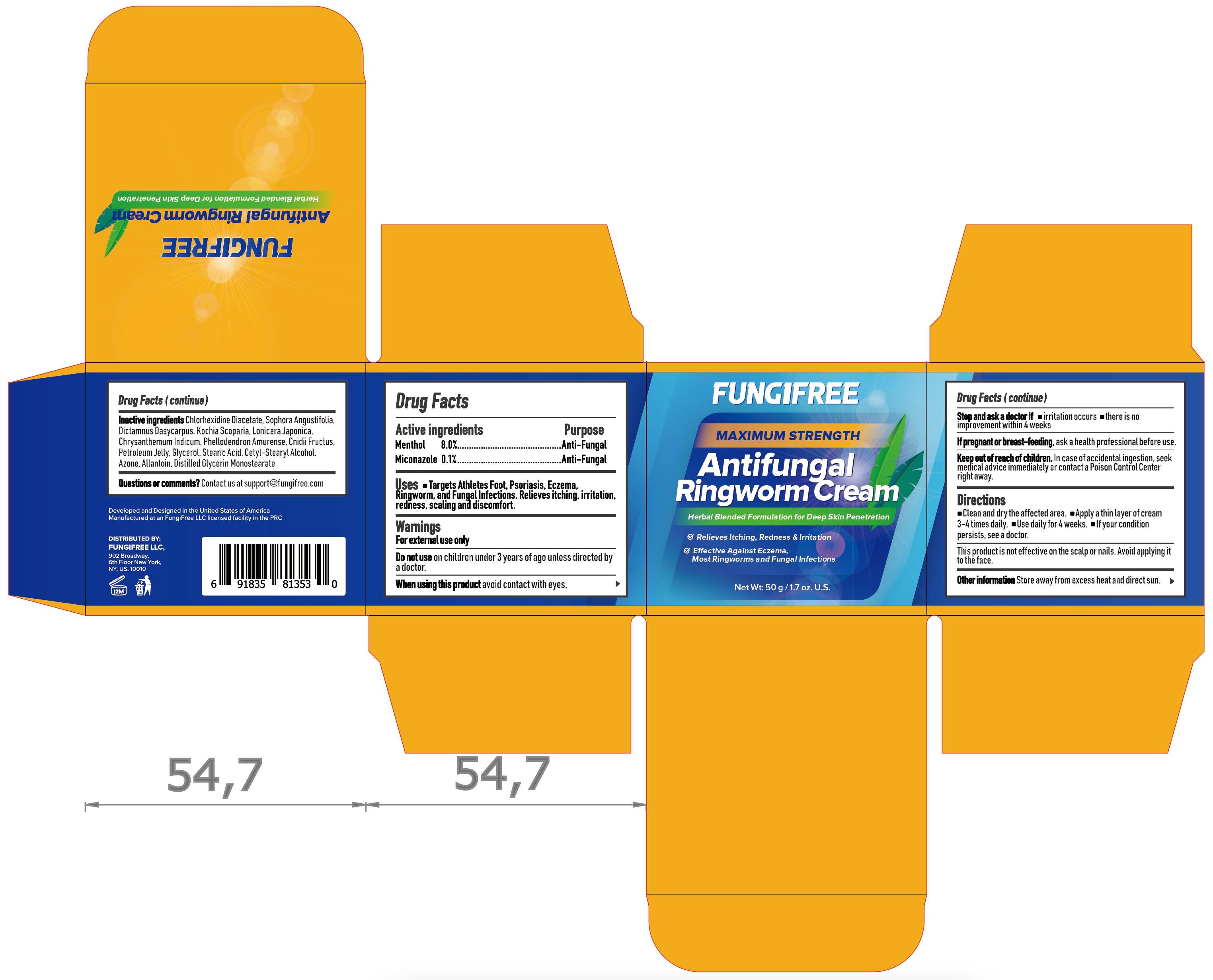 DRUG LABEL: Antifungal Ringworm Cream
NDC: 85248-007 | Form: CREAM
Manufacturer: Jiangxi Yudexi Pharmaceutical Co., LTD
Category: otc | Type: HUMAN OTC DRUG LABEL
Date: 20250528

ACTIVE INGREDIENTS: MICONAZOLE 0.1 g/100 g; MENTHOL, UNSPECIFIED FORM 8 g/100 g
INACTIVE INGREDIENTS: GLYCERYL MONOSTEARATE; LONICERA JAPONICA STEM; CHRYSANTHEMUM INDICUM FLOWER; STEARIC ACID; PHELLODENDRON AMURENSE BARK; CNIDIUM MONNIERI FRUIT; SOPHORA FLAVESCENS ROOT; PETROLATUM; LAUROCAPRAM; ALLANTOIN; DICTAMNUS DASYCARPUS ROOT; GLYCERIN; CETOSTEARYL ALCOHOL; CHLORHEXIDINE ACETATE; BASSIA SCOPARIA WHOLE

FUNGIFREE ANTIFUNGAL RINGWORM CREAM

Drug facts

Active ingredients Purpose

Menthol 8.0%…............................…………………..………………….Anti-Fungal
Miconazole 0.1%…............................…………….……..…………….Anti-Fungal

Uses

Targets Athletes Foot, Psoriasis, Eczema, Ringworm, and Fungal Infections. Relieves itching, irritation, redness, scaling and discomfort.

DOSAGE AND ADMINISTRATION

For external use only

Do not use on children under 3 years of age unless directed by a doctor.

When using this product avoid contact with eyes.

ASK DOCTOR

Stop and ask a doctor if - irritation occurs - there is no improvement within 4 weeks

PREGNANCY OR BREAST FEEDING

If pregnant or breast-feeding, ask a health professional before use.

Keep out of reach of children. In case of accidental ingestion, seek medical advice immediately or contact a Poison Control Center right away.

Warnings

Directions

- Clean and dry the affected area.
- Apply a thin layer of cream 3-4 times daily.
- Use daily for 4 weeks.
- If your condition persists, see a doctor.
- This product is not effective on the scalp or nails. Avoid applying it to the face.

Other information

Store away from excess heat and direct sun.

Inactive ingredients

Chlorhexidine Diacetate, Sophora Angustifolia, Dictamnus Dasycarpus, Kochia Scoparia, Lonicera Japonica, Chrysanthemum Indicum, Phellodendron Amurense, Cnidii Fructus, Petroleum Jelly, Glycerol, Stearic Acid, Cetostearyl Alcohol, Azone, Allantoin, Glycerol Monostearate